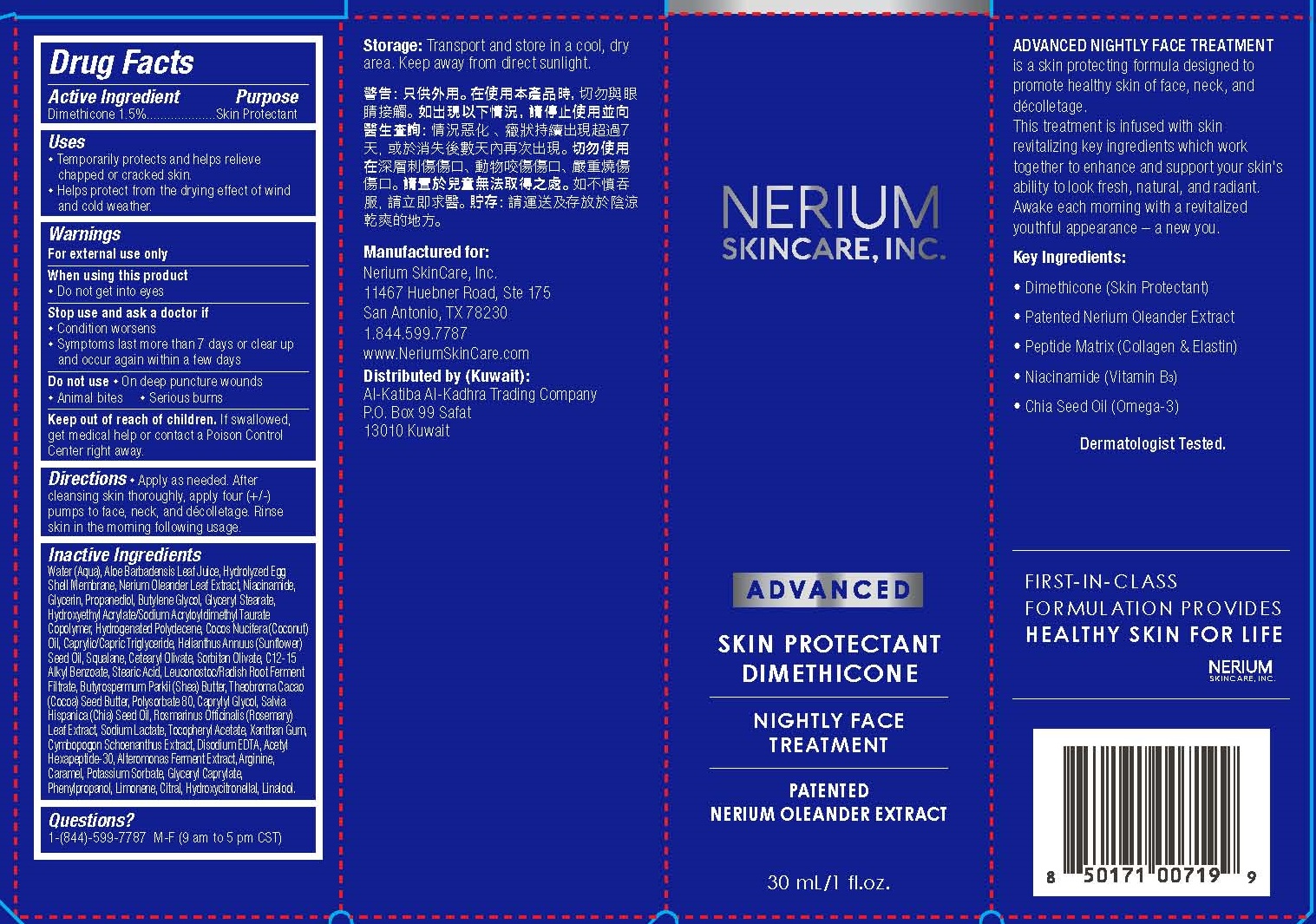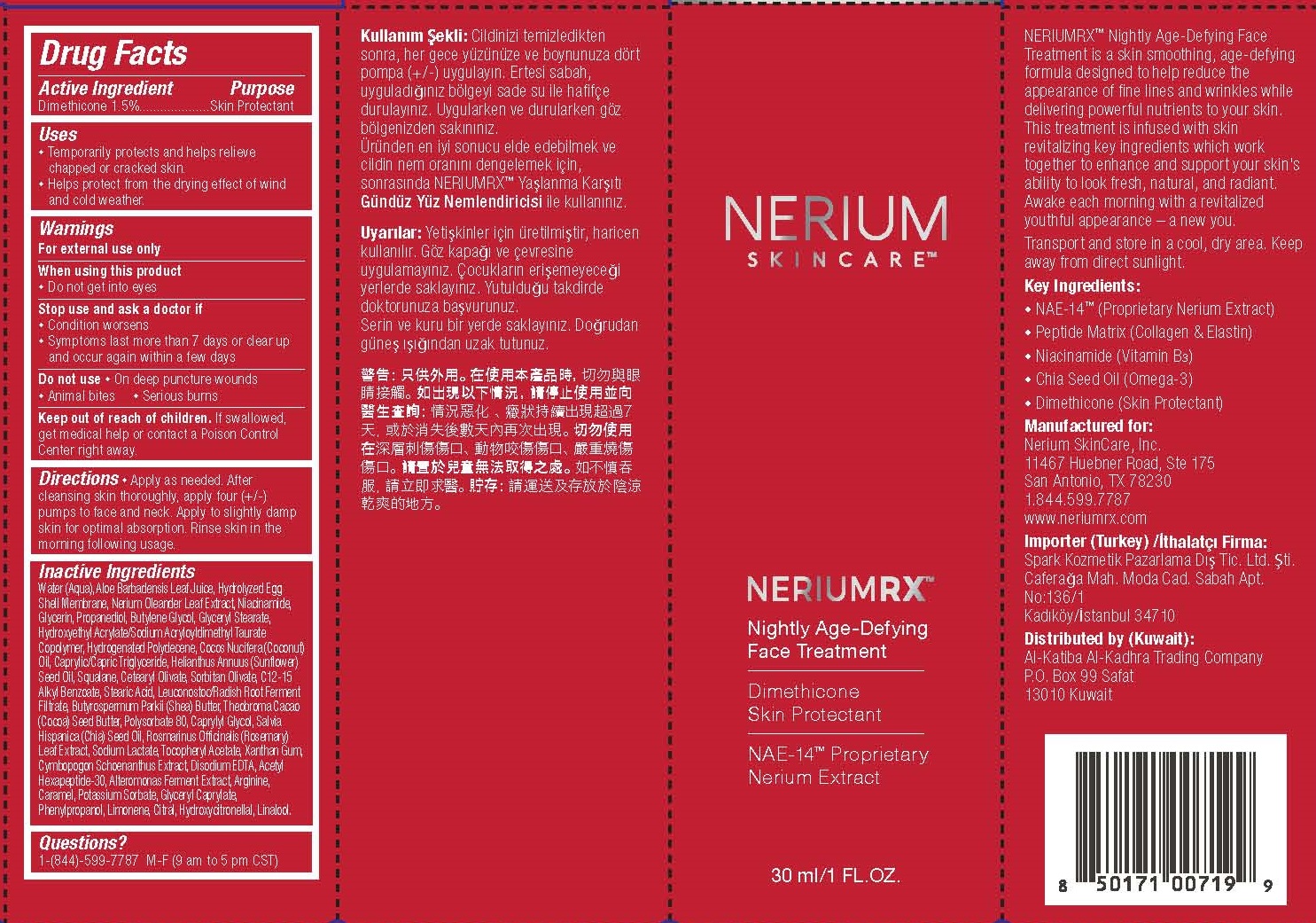 DRUG LABEL: NIGHTLY FACE TREATMENT - DIMETHICONE
NDC: 71593-101 | Form: CREAM
Manufacturer: ARG LABORATORIES INC
Category: otc | Type: HUMAN OTC DRUG LABEL
Date: 20230109

ACTIVE INGREDIENTS: DIMETHICONE 1.5 g/100 mL
INACTIVE INGREDIENTS: WATER; ALOE VERA LEAF; EGG SHELL MEMBRANE; NERIUM OLEANDER LEAF; NIACINAMIDE; GLYCERIN; PROPANEDIOL; BUTYLENE GLYCOL; GLYCERYL MONOSTEARATE; HYDROXYETHYL ACRYLATE/SODIUM ACRYLOYLDIMETHYL TAURATE COPOLYMER (45000 MPA.S AT 1%); HYDROGENATED POLYDECENE (550 MW); COCONUT OIL; MEDIUM-CHAIN TRIGLYCERIDES; SUNFLOWER OIL; SQUALANE; CETEARYL OLIVATE; SORBITAN OLIVATE; ALKYL (C12-15) BENZOATE; STEARIC ACID; LEUCONOSTOC/RADISH ROOT FERMENT FILTRATE; SHEA BUTTER; COCOA BUTTER; POLYSORBATE 80; CAPRYLYL GLYCOL; SALVIA HISPANICA SEED; ROSEMARY; SODIUM LACTATE; .ALPHA.-TOCOPHEROL ACETATE; XANTHAN GUM; CYMBOPOGON SCHOENANTHUS WHOLE; EDETATE DISODIUM; ACETYL HEXAPEPTIDE-49; ALTEROMONAS MACLEODII; ARGININE; CARAMEL; POTASSIUM SORBATE; GLYCERYL CAPRYLATE; PHENYLPROPANOL; LIMONENE, (+)-; CITRAL; HYDROXYCITRONELLAL; LINALOOL, (+)-

ARG LABORATORIES (as CMO) - NIGHTLY FACE TREATMENT - DIMETHICONE CREAM (71593-101)

ACTIVE INGREDIENT

DIMETHICONE 1.5%

PURPOSE

SKIN PROTECTANT

USES

• Temporarily protects and helps relieve chapped or cracked skin.
• Helps protect from the drying effect of wind and cold weather.

WARNINGS

For external use only

When using this product
• Do not get into eyes

Stop use and ask a doctor if
• Condition worsens

• Symptoms last more than 7 days or clear up and occur again within a few days

Do not use

• On deep puncture wounds

• Animal bites

• Serious burns

Keep out of reach of children. If swallowed, get medical help or contact a Poison Control Center right away.

DIRECTIONS

• Apply as needed. After cleansing skin thoroughly, apply four (+/-) pumps to face and neck. Apply to slightly damp skin for optimal absorption. Rinse skin in the morning following usage.

INACTIVE INGREDIENTS

WATER (AQUA), ALOE BARBADENSIS LEAF JUICE, HYDROLYZED EGG SHELL MEMBRANE, NERIUM OLEANDER LEAF EXTRACT, NIACINAMIDE GLYCERIN, PROPANEDIOL,BUTYLENE GLYCOL, GLYCERYL STEARATE, Hydroxyethylacrylate/Sodium
Acryloyldimethyltaurate Copolymer, Hydrogenated Polydecene, Cocos Nucifera (Coconut) Oil, Caprylic/Capric Triglyceride, HELIANTHUS ANNUUS (SUNFLOWER) SEED OIL, SQUALANE, Cetearyl Olivate, Sorbitan Olivate, C12-15 Alkyl Benzoate, Stearic Acid, LEUCONOSTOC/RADISH ROOT FERMENT, Butyrospermum Parkii (Shea) Butter, Theobroma Cacao (Cocoa) Seed Butter, Polysorbate 80, CAPRYLYL GLYCOL, SALVIA HISPANICA (CHIA) SEED OIL, ROSMARINUS OFFICINALIS (ROSEMARY) LEAF EXTRACT, Sodium Lactate, Tocopheryl Acetate, Xanthan Gum, Cymbopogon Schoenanthus Extract, Disodium EDTA, Acetyl Hexapeptide-30, Alteromonas Ferment Extract, Arginine, Caramel, POTASSIUM SORBATE, GLYCERYL CAPRYLATE, PHENYLPROPANOL, Limonene, Citral, Hydroxycitronellal, Linalool.

QUESTIONS?

1-(844)-599-7787 M-F (9 AM TO 5 PM CST)